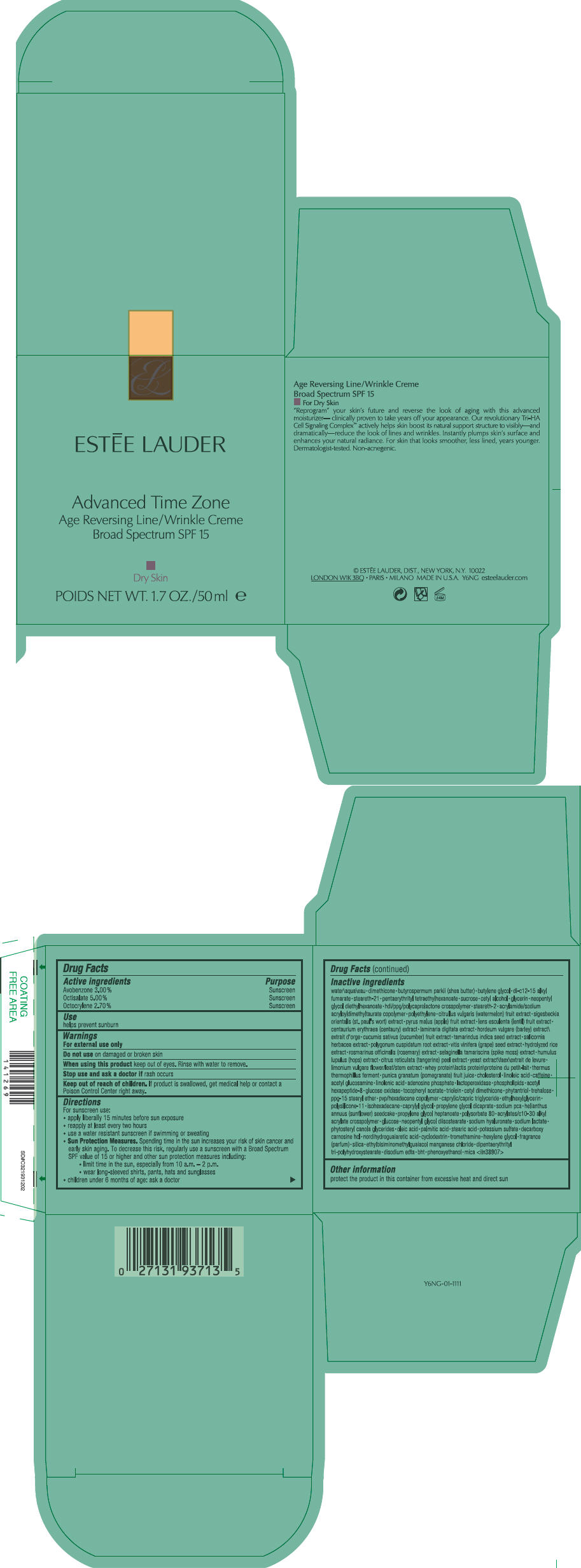 DRUG LABEL: ADVANCED TIME ZONE AGE REVERSING 
NDC: 11559-020 | Form: CREAM
Manufacturer: ESTEE LAUDER INC
Category: otc | Type: HUMAN OTC DRUG LABEL
Date: 20120904

ACTIVE INGREDIENTS: AVOBENZONE 3 mL/100 mL; OCTISALATE 5 mL/100 mL; OCTOCRYLENE 2.7 mL/100 mL
INACTIVE INGREDIENTS: water; dimethicone; shea butter; butylene glycol; di-c12-15 alkyl fumarate; steareth-21; pentaerythrityl tetraethylhexanoate; sucrose; cetyl alcohol; glycerin; neopentyl glycol diethylhexanoate; steareth-2; high density polyethylene; watermelon; apple; lens culinaris fruit; centaurium erythraea; laminaria digitata; barley; cucumber; tamarind seed; salicornia europaea; polygonum cuspidatum root; vitis vinifera seed; rosemary; selaginella tamariscina; hops; tangerine peel; yeast; limonium vulgare flowering top; pomegranate juice; cholesterol; linoleic acid; caffeine; n-acetylglucosamine; linolenic acid; adenosine phosphate; acetyl hexapeptide-8; glucose oxidase; .alpha.-tocopherol acetate; glyceryl trioleate; phytantriol; trehalose; ppg-15 stearyl ether; isohexadecane; medium-chain triglycerides; ethylhexylglycerin; caprylyl glycol; helianthus annuus seedcake; propylene glycol dicaprate; propylene glycol heptanoate; sodium pyrrolidone carboxylate; dextrose; neopentyl glycol diisostearate; hyaluronate sodium; sodium lactate; oleic acid; palmitic acid; stearic acid; potassium sulfate; decarboxy carnosine hydrochloride; masoprocol; tromethamine; hexylene glycol; silicon dioxide; edetate disodium; butylated hydroxytoluene; phenoxyethanol; mica

ADVANCED TIME ZONE AGE REVERSING / LINE WRINKLE CRÈME BROAD SPECTRUM SPF 15 DRY SKIN

Drug Facts

ACTIVE INGREDIENT

Active ingredients | Purpose
Avobenzone 3.00% | Sunscreen
Octisalate 5.00% | Sunscreen
Octocrylene 2.70% | Sunscreen

Use

helps prevent sunburn

Warnings

For external use only

Do not use on damaged or broken skin

When using this product keep out of eyes. Rinse with water to remove.

Stop use and ask a doctor if rash occurs

Keep out of reach of children. If product is swallowed, get medical help or contact a Poison Control Center right away.

Directions

For sunscreen use:

- apply liberally 15 minutes before sun exposure
- reapply at least every two hours
- use a water resistant sunscreen if swimming or sweating
- Sun Protection Measures. Spending time in the sun increases your risk of skin cancer and early skin aging. To decrease this risk, regularly use a sunscreen with a Broad Spectrum SPF value of 15 or higher and other sun protection measures including:
  - limit time in the sun, especially from 10 a.m. – 2 p.m.
  - wear long-sleeved shirts, pants, hats and sunglasses
- children under 6 months of age: ask a doctor

Inactive ingredients

water\aqua\eau • dimethicone • butyrospermum parkii (shea butter) • butylene glycol • di-c12-15 alkyl fumarate • steareth-21 • pentaerythrityl tetraethylhexanoate • sucrose • cetyl alcohol • glycerin • neopentyl glycol diethylhexanoate • hdi/ppg/polycaprolactone crosspolymer • steareth-2 • acrylamide/sodium acryloyldimethyltaurate copolymer • polyethylene • citrullus vulgaris (watermelon) fruit extract • sigesbeckia orientalis (st. paul's wort) extract • pyrus malus (apple) fruit extract • lens esculenta (lentil) fruit extract • centaurium erythraea (centaury) extract • laminaria digitata extract • hordeum vulgare (barley) extract\extrait d'orge • cucumis sativus (cucumber) fruit extract • tamarindus indica seed extract • salicornia herbacea extract • polygonum cuspidatum root extract • vitis vinifera (grape) seed extract • hydrolyzed rice extract • rosmarinus officinalis (rosemary) extract • selaginella tamariscina (spike moss) extract • humulus lupulus (hops) extract • citrus reticulata (tangerine) peel extract • yeast extract\faex\extrait de levure • limonium vulgare flower/leaf/stem extract • whey protein\lactis protein\proteine du petit-lait • thermus thermophillus ferment • punica granatum (pomegranate) fruit juice • cholesterol • linoleic acid • caffeine • acetyl glucosamine • linolenic acid • adenosine phosphate • lactoperoxidase • phospholipids • acetyl hexapeptide-8 • glucose oxidase • tocopheryl acetate • triolein • cetyl dimethicone • phytantriol • trehalose • ppg-15 stearyl ether • pvp/hexadecene copolymer • caprylic/capric triglyceride • ethylhexylglycerin • polysilicone-11 • isohexadecane • caprylyl glycol • propylene glycol dicaprate • sodium pca • helianthus annuus (sunflower) seedcake • propylene glycol heptanoate • polysorbate 80 • acrylates/c10-30 alkyl acrylate crosspolymer • glucose • neopentyl glycol diisostearate • sodium hyaluronate • sodium lactate • phytosteryl canola glycerides • oleic acid • palmitic acid • stearic acid • potassium sulfate • decarboxy carnosine hcl • nordihydroguaiaretic acid • cyclodextrin • tromethamine • hexylene glycol • fragrance (parfum) • silica • ethylbisiminomethylguaiacol manganese chloride • dipentaerythrityl tri-polyhydroxystearate • disodium edta • bht • phenoxyethanol • mica <iln38907>

Other information

protect the product in this container from excessive heat and direct sun

ESTEĒ LAUDER, DIST., NEW YORK, N.Y. 10022

PRINCIPAL DISPLAY PANEL - 50 ml Jar Carton

EL

ESTĒE LAUDER

Advanced Time Zone
Age Reversing Line/Wrinkle Creme
Broad Spectrum SPF 15

Dry Skin

POIDS NET WT. 1.7 OZ./50 ml e